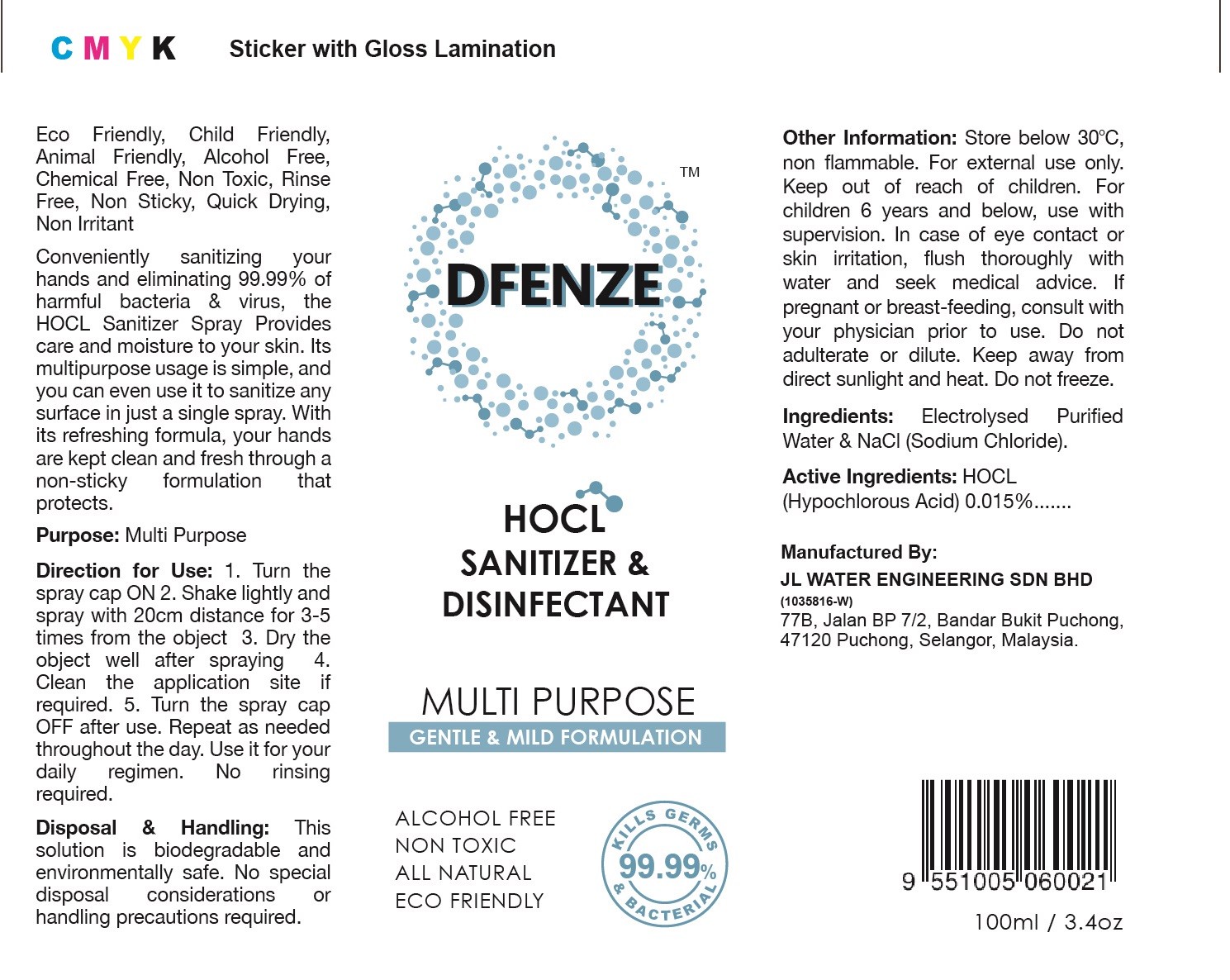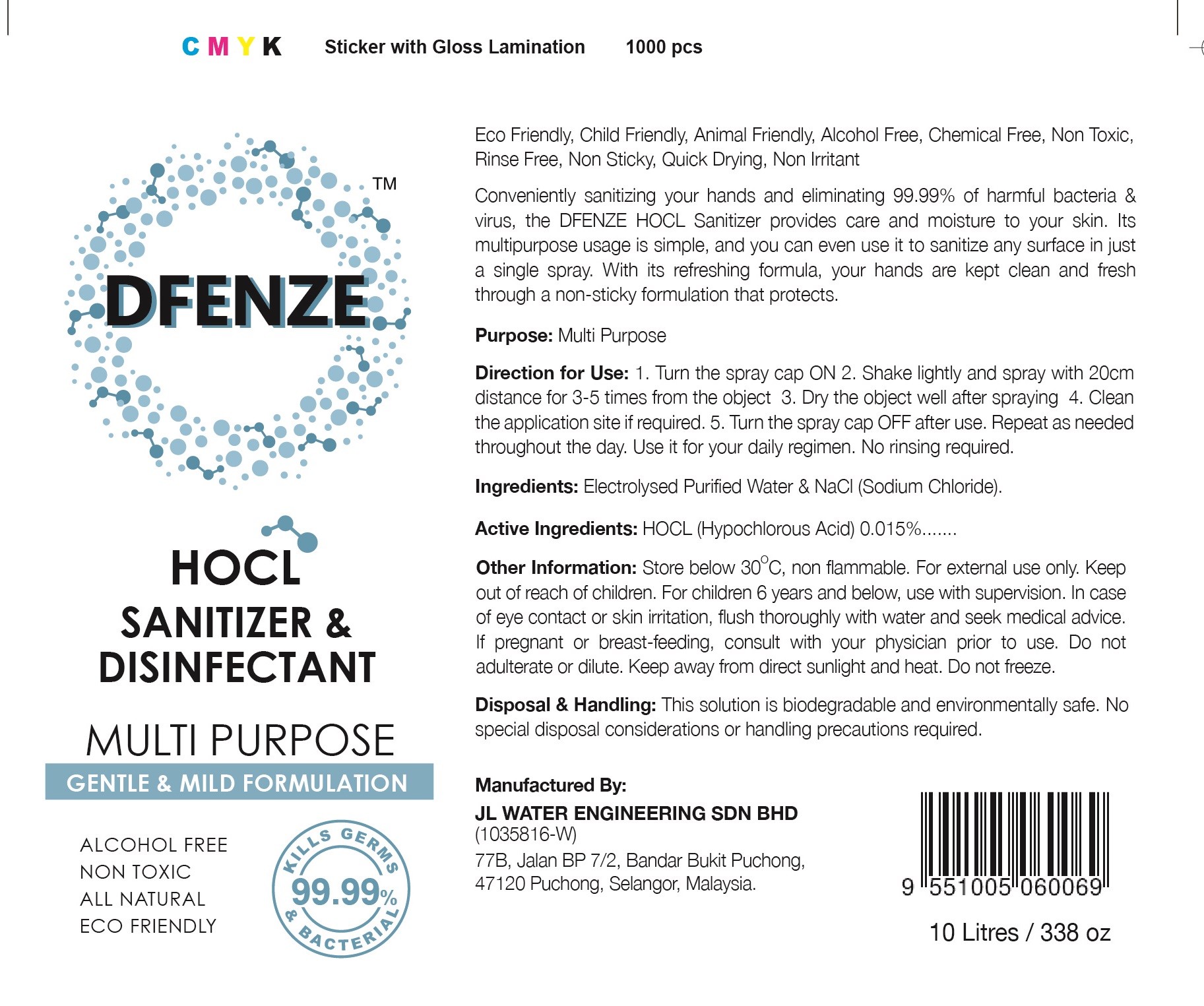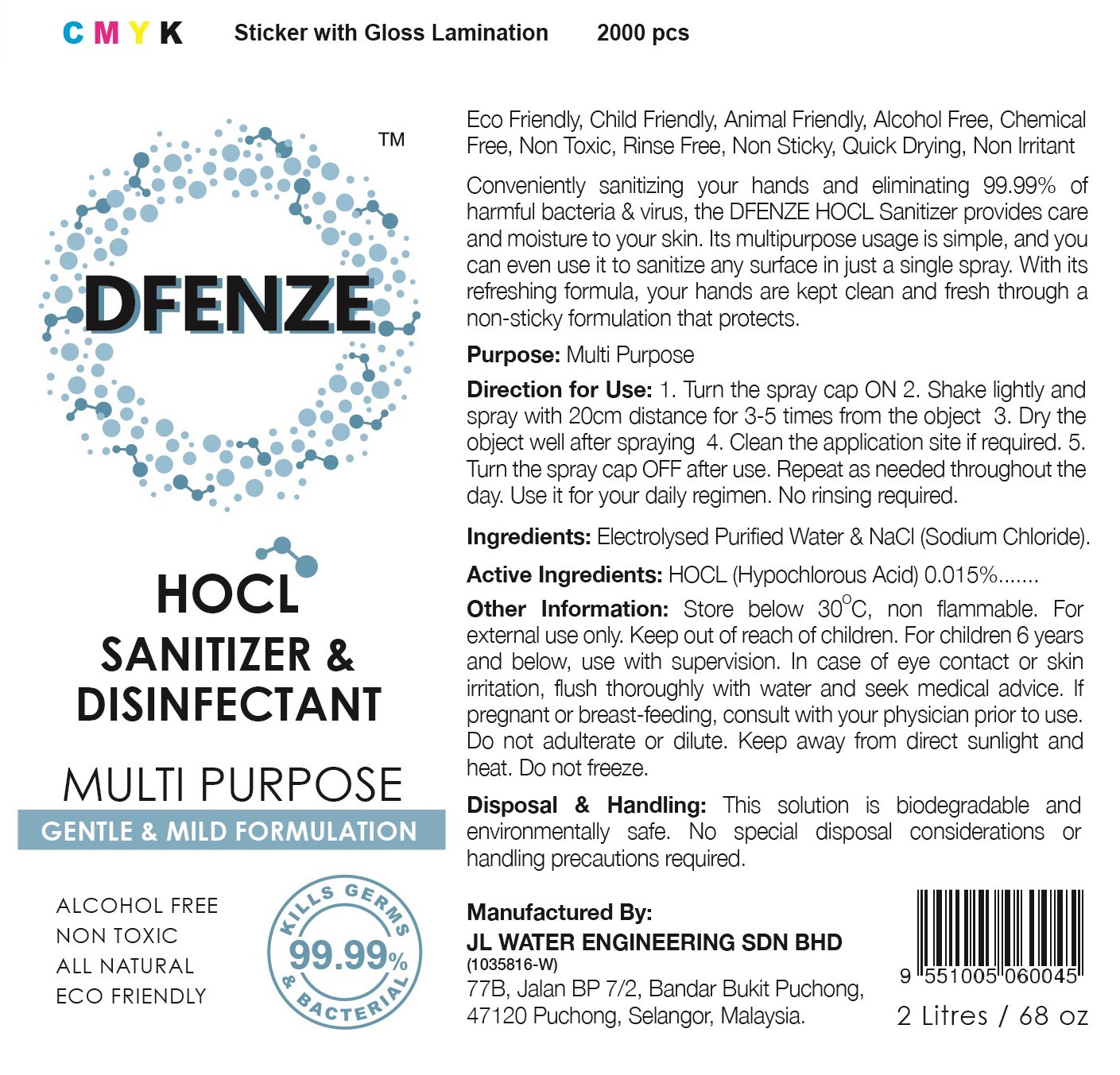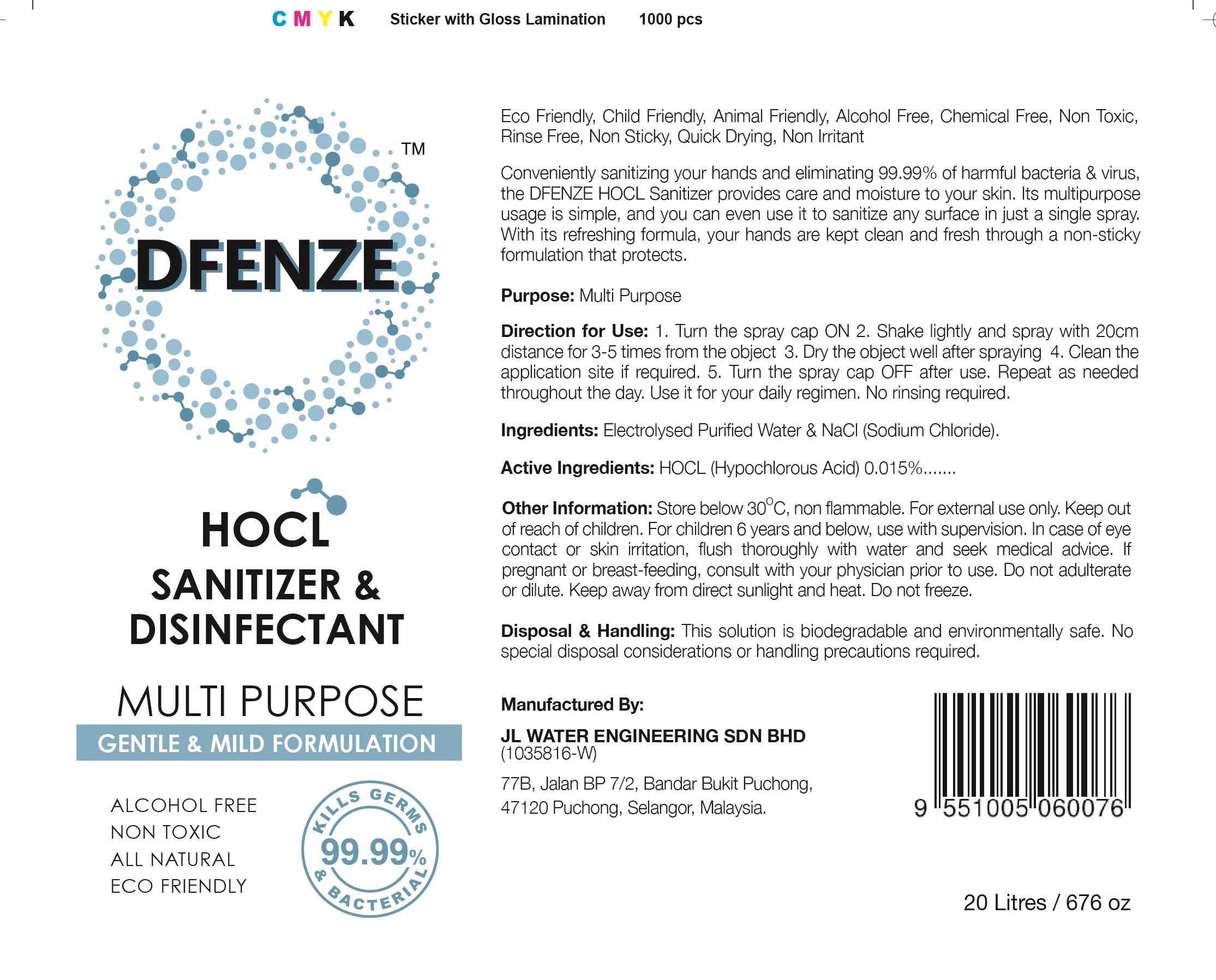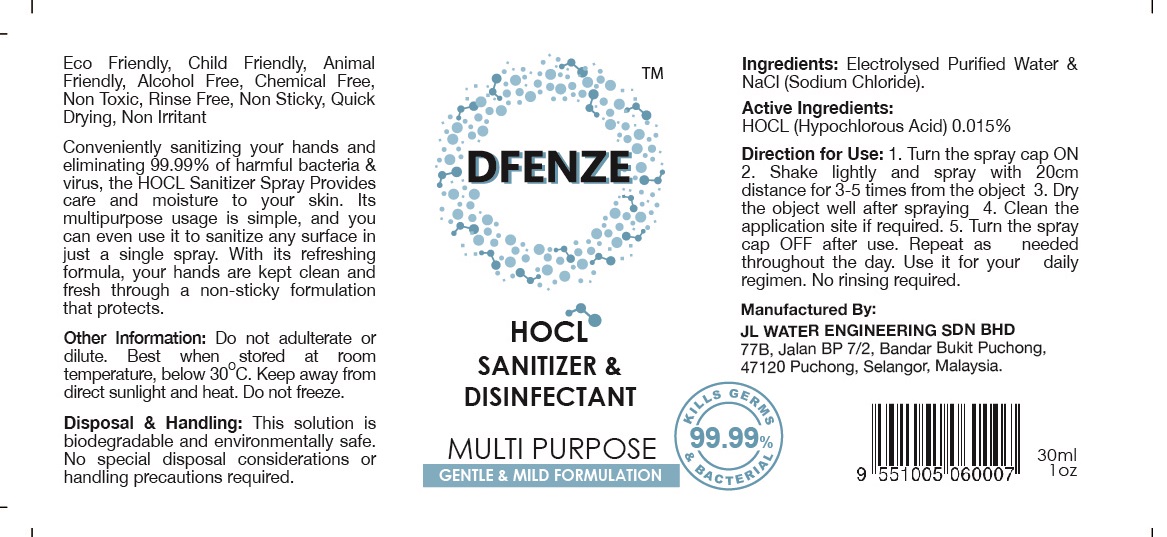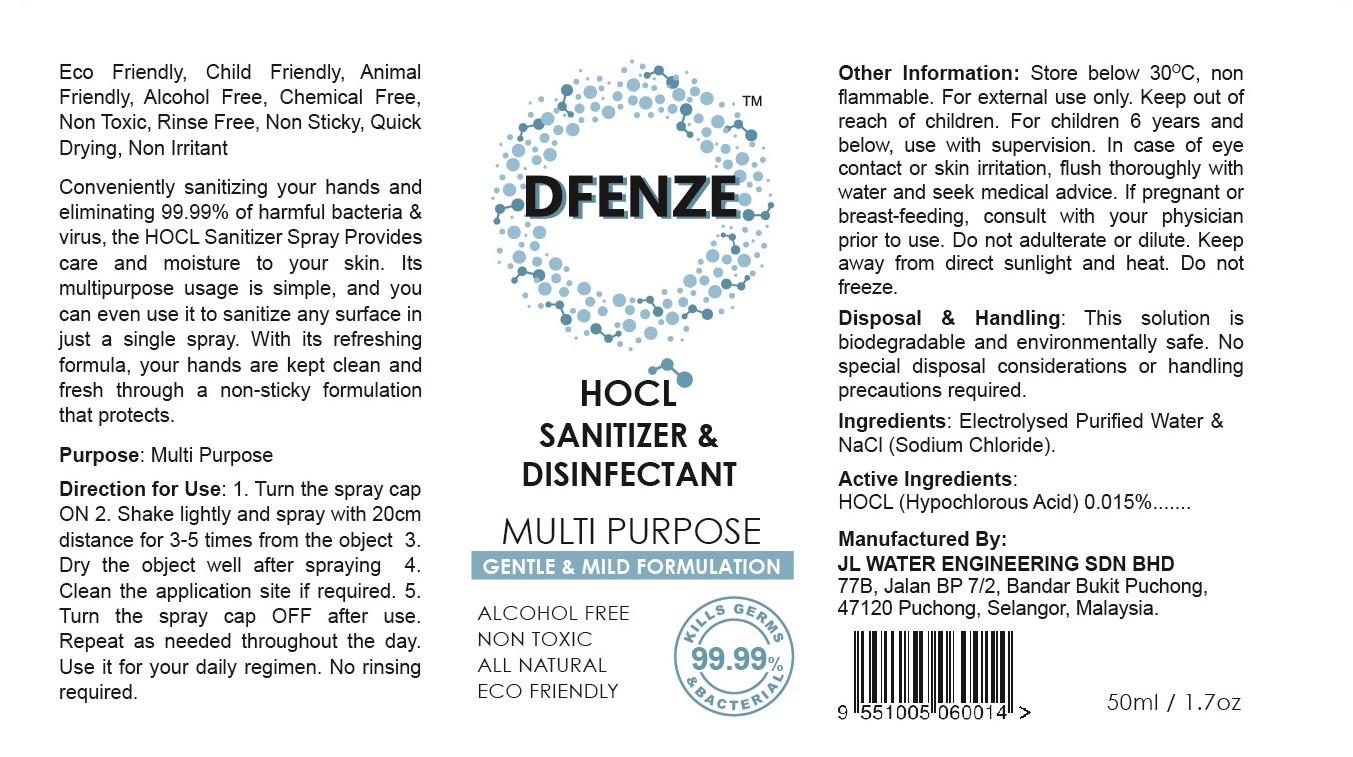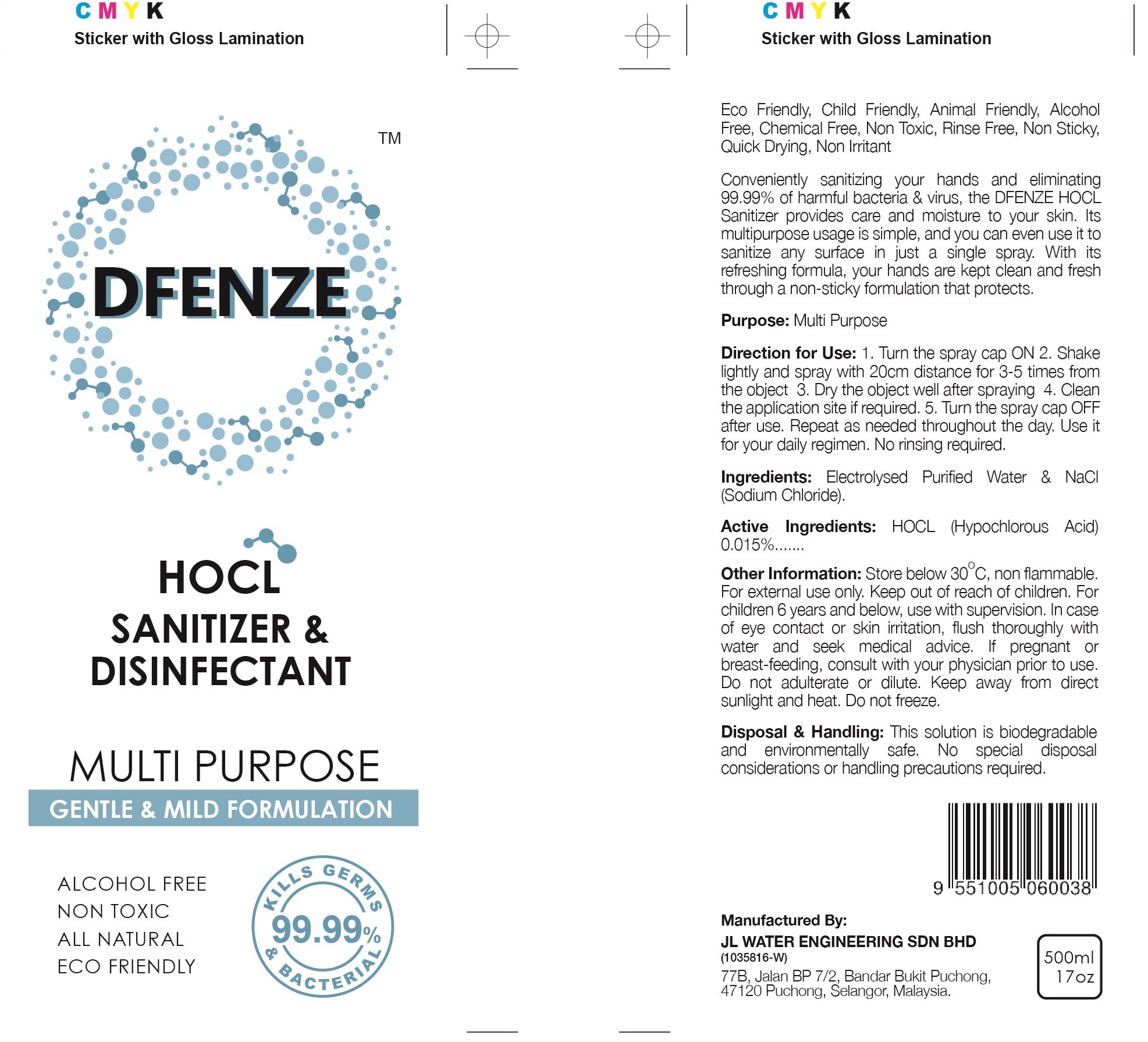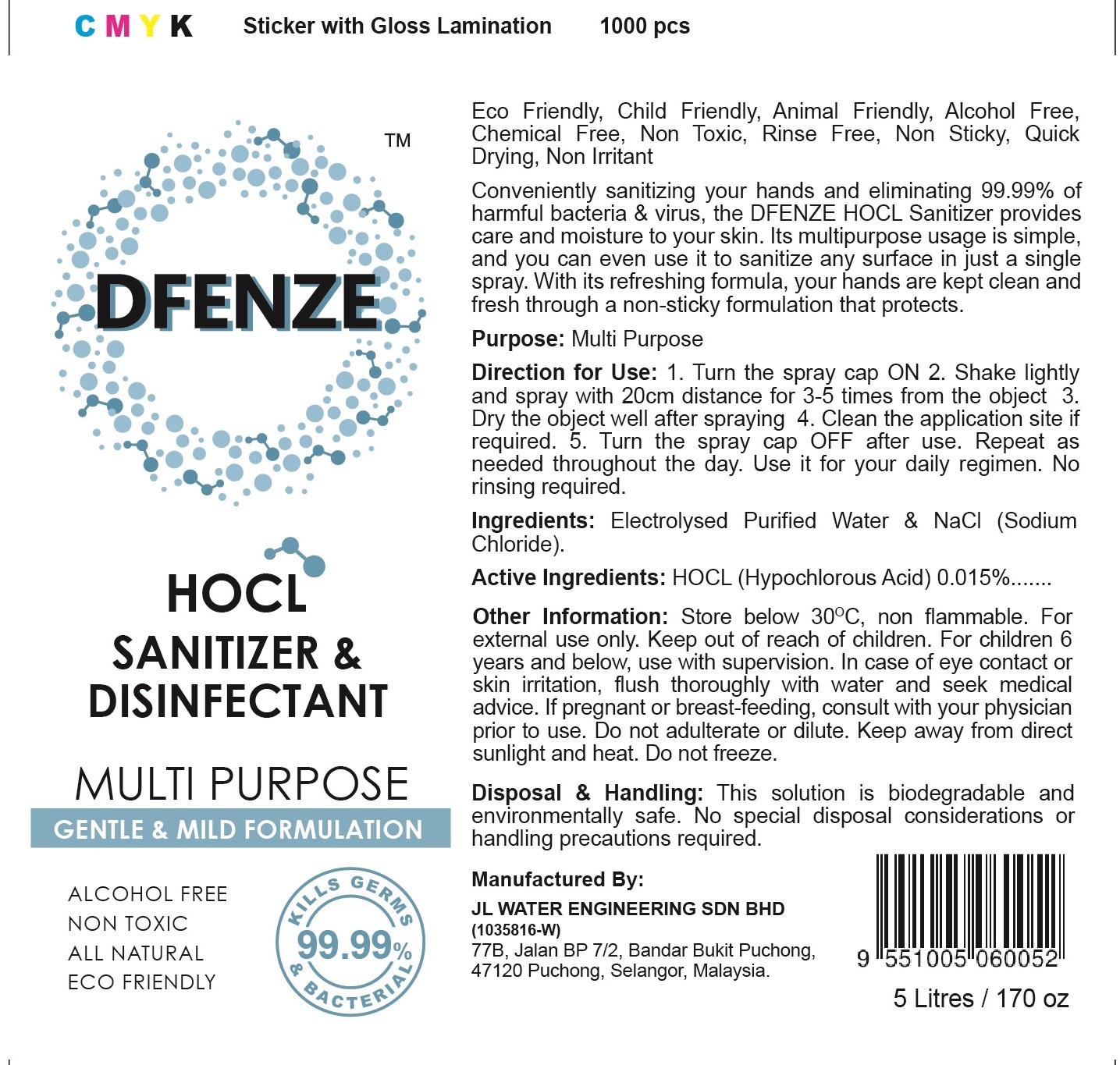 DRUG LABEL: Dfenze HOCL Sanitizer and Disinfectant
NDC: 79762-001 | Form: LIQUID
Manufacturer: JL WATER ENGINEERING SDN. BHD.
Category: otc | Type: HUMAN OTC DRUG LABEL
Date: 20200721

ACTIVE INGREDIENTS: HYPOCHLOROUS ACID 0.015 g/100 mL
INACTIVE INGREDIENTS: SODIUM CHLORIDE; WATER

Dfenze HOCL Sanitizer & Disinfectant

Active Ingredient(s)

HOCL (Hypochlorous Acid) 0.015%

Purpose

Multi Purpose

Warnings

For external use only.

Do not use

- Do not adulterate or dilute. Keep away from direct sunlight and heat. Do not freeze.

WHEN USING

For children 6 years and below, use with supervision. In case of eye contact or skin irritation, flush thoroughly with water and seek medical advice. If pregnant or breast-feeding, consult with your physician prior to use.

STOP USE

/

Keep out of reach of children.

Directions

1. Turn the spray cap ON
2. Shake lightly and spray with 20cm distance for 3-5 times from the object
3. Dry the object well after spraying
4. Clean the application site if required.
5. Turn the spray cap OFF after use. Repeat as needed throughout the day. Use it for your daily regimen. No rinsing required.

Other information

Store below 300C, non flammable.

Inactive ingredients

Electrolysed Purified Water & NaCl (Sodium Chloride).

INDICATIONS AND USAGE

1. Turn the spray cap ON
2. Shake lightly and spray with 20cm distance for 3-5 times from the object
3. Dry the object well after spraying
4. Clean the application site if required.
5. Turn the spray cap OFF after use. Repeat as needed throughout the day. Use it for your daily regimen. No rinsing required.